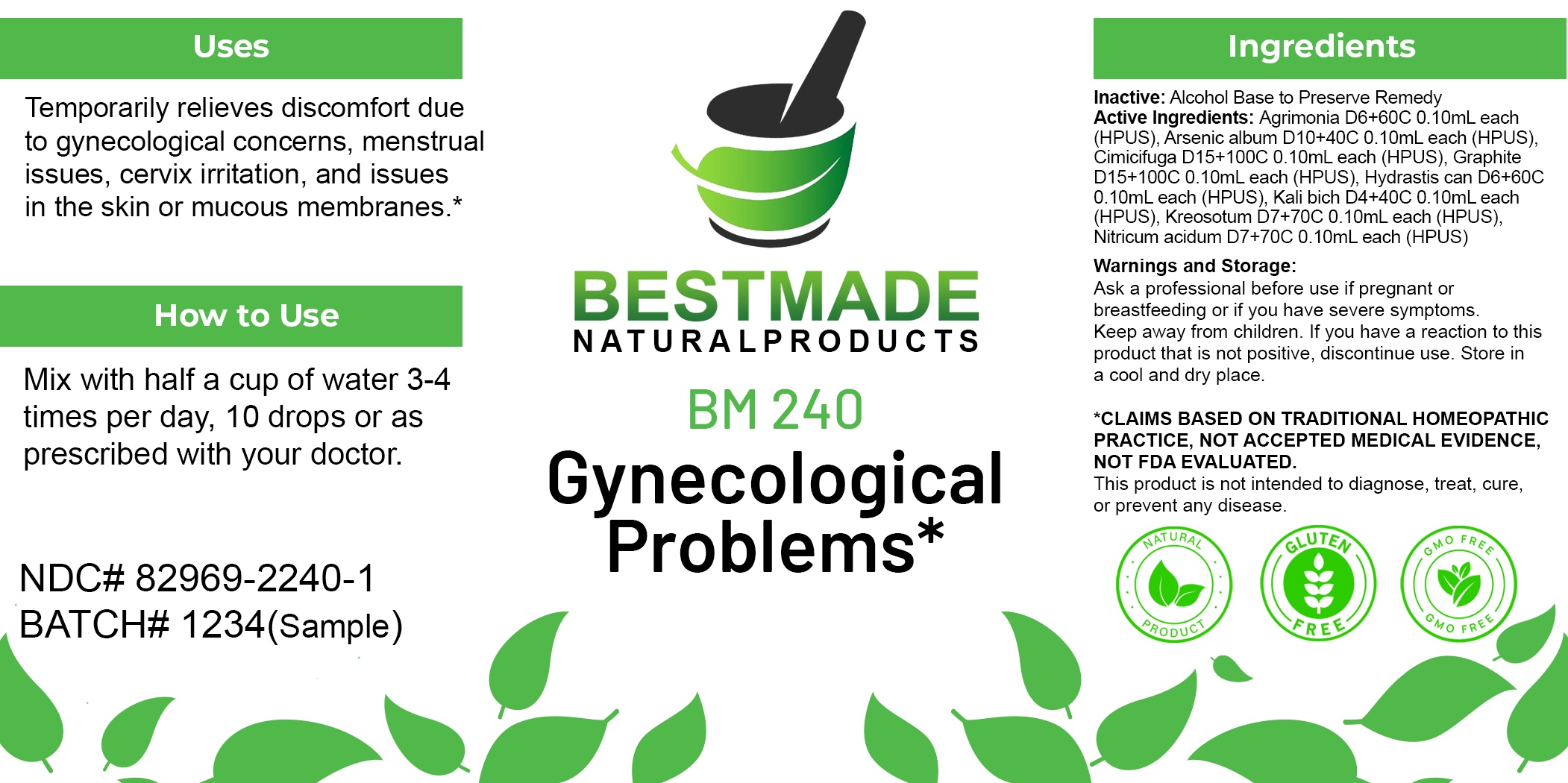 DRUG LABEL: Bestmade Natural Products BM240
NDC: 82969-2240 | Form: LIQUID
Manufacturer: Bestmade Natural Products
Category: homeopathic | Type: HUMAN OTC DRUG LABEL
Date: 20250304

ACTIVE INGREDIENTS: AGRIMONIA EUPATORIA 30 [hp_C]/30 [hp_C]; NITRIC ACID 30 [hp_C]/30 [hp_C]; POTASSIUM DICHROMATE 30 [hp_C]/30 [hp_C]; GRAPHITE 30 [hp_C]/30 [hp_C]; ARSENIC TRIOXIDE 30 [hp_C]/30 [hp_C]; BLACK COHOSH 30 [hp_C]/30 [hp_C]; GOLDENSEAL 30 [hp_C]/30 [hp_C]; WOOD CREOSOTE 30 [hp_C]/30 [hp_C]
INACTIVE INGREDIENTS: ALCOHOL 30 [hp_C]/30 [hp_C]

BM240

DOSAGE AND ADMINISTRATION

How to Use

Mix with half a cup of water 3-4 times per day. Ages 12 or older, 10 drops. Ages 12-2, 5 drops. Ages 2 and under, consult your Doctor.

Inactive:

Alcohol Base to Preserve Product

ACTIVE INGREDIENT

Active Ingredients: Agrimonia D6+60C 0.10mL each (HPUS), Arsenic album D10+40C 0.10mL each (HPUS), Cimicifuga D15+100C 0.10mL each (HPUS), Graphite D15+100C 0.10mL each (HPUS), Hydrastis can D6+60C 0.10mL each (HPUS), Kali bich D4+40C 0.10mL each (HPUS), Kreosotum D7+70C 0.10mL each (HPUS), Nitricum acidum D7+70C 0.10mL each (HPUS)

KEEP OUT OF REACH OF CHILDREN

Warnings and Storage:

Ask a professional before use if pregnant or breastfeeding or if you have severe symptoms.

Keep away from children. If you have a reaction to this product that is not positive, discontinue use. Store in a cool and dry place

*CLAIMS BASED ON TRADITIONAL HOMEOPATHIC PRACTICE, NOT ACCEPTED MEDICAL EVIDENCE NOT FDA EVALUATED.
This product is not intended to diagnose, treat, cure, or prevent any disease.

Warnings and Storage:

Ask a professional before use if pregnant or breastfeeding or if you have severe symptoms.

Keep away from children. If you have a reaction to this product that is not positive, discontinue use. Store in a cool and dry place

*CLAIMS BASED ON TRADITIONAL HOMEOPATHIC PRACTICE, NOT ACCEPTED MEDICAL EVIDENCE NOT FDA EVALUATED.
This product is not intended to diagnose, treat, cure, or prevent any disease.

Uses
Temporarily relieves discomfort due to gynecological concerns, menstrual issues, cervix irritation, and issues in the skin or mucous membranes.*

Uses
Temporarily relieves discomfort due to gynecological concerns, menstrual issues, cervix irritation, and issues in the skin or mucous membranes.*

Entire package label